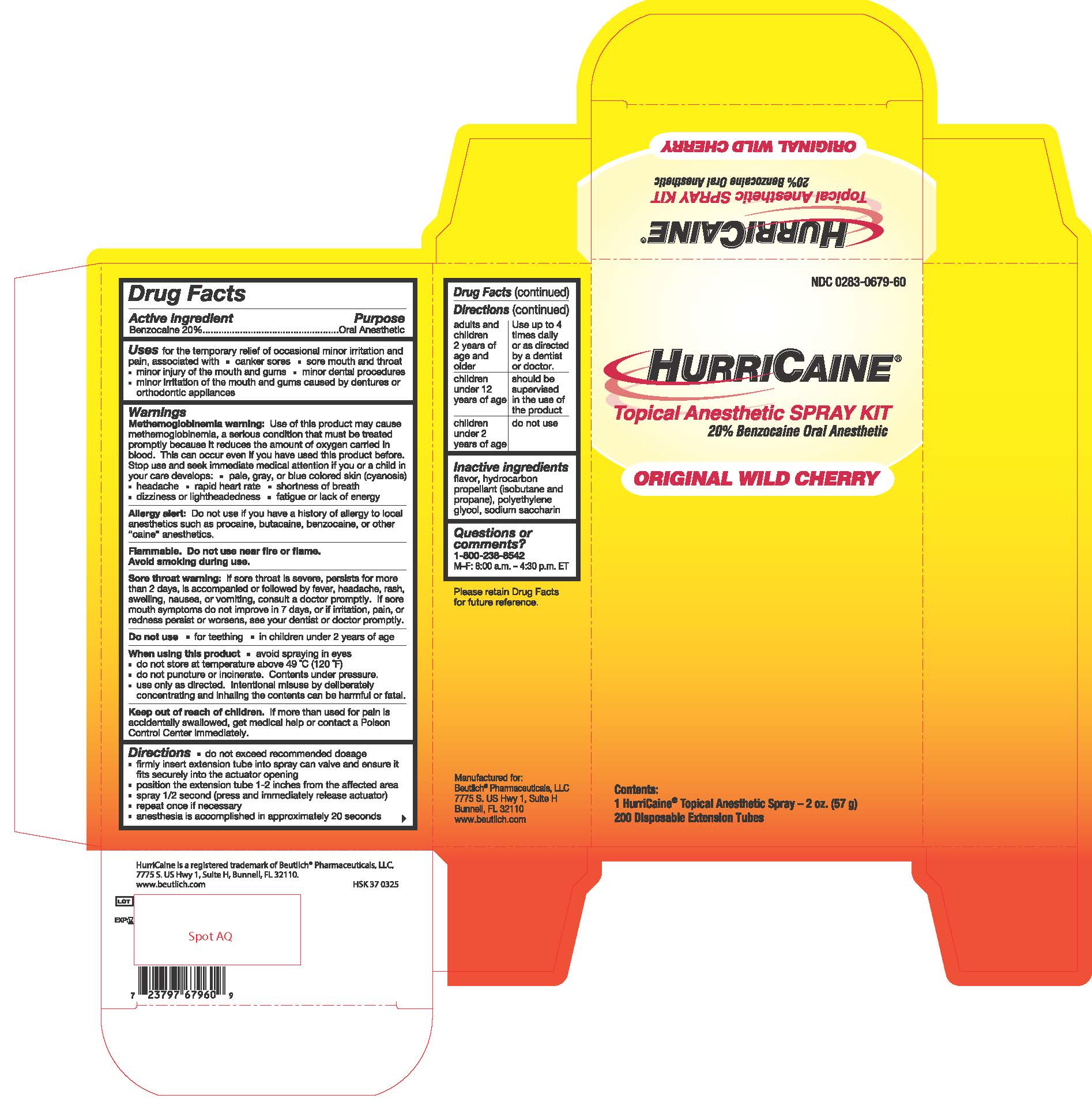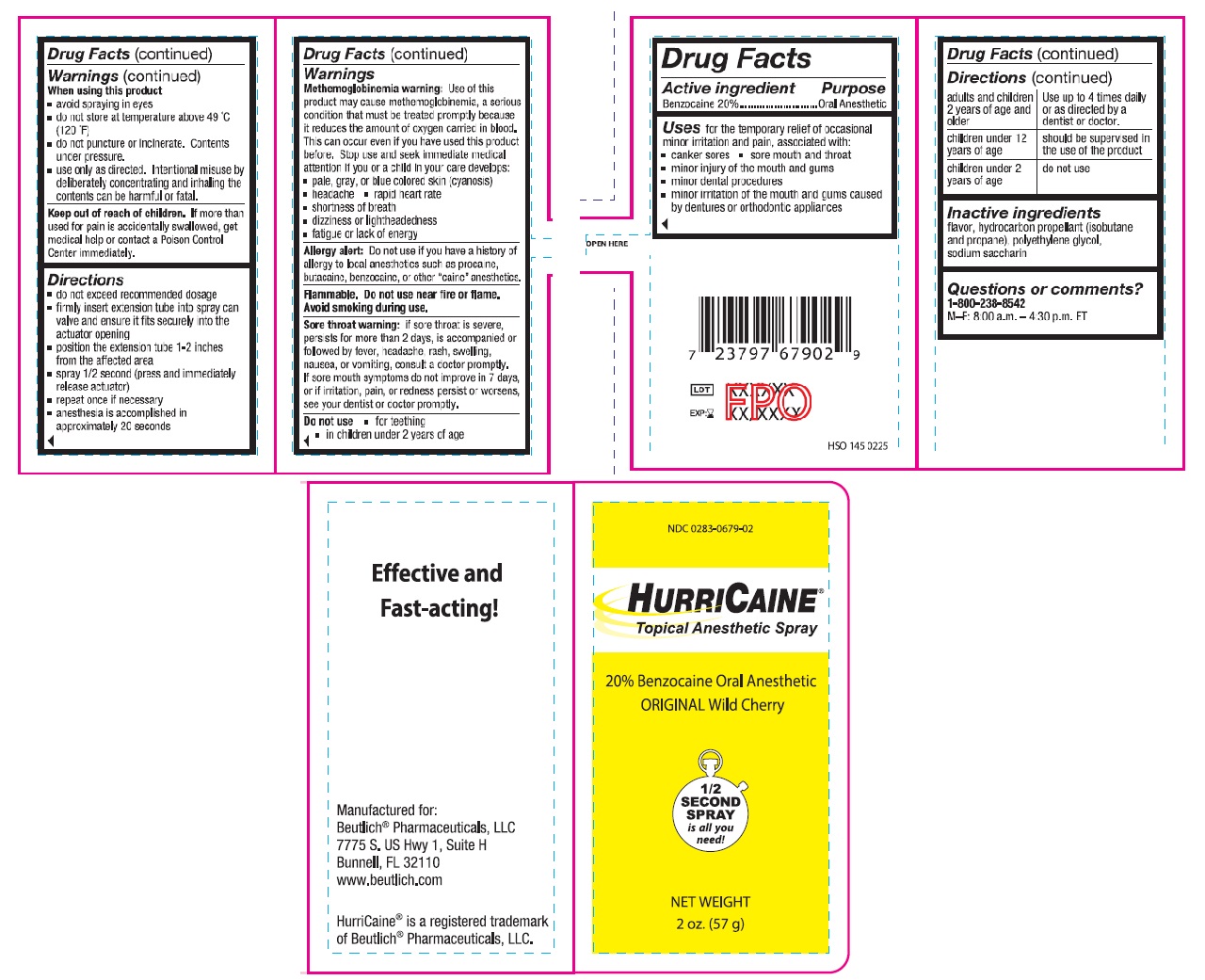 DRUG LABEL: HurriCaine
NDC: 0283-0679 | Form: SPRAY
Manufacturer: Beutlich Pharmaceuticals, LLC
Category: otc | Type: HUMAN OTC DRUG LABEL
Date: 20250520

ACTIVE INGREDIENTS: BENZOCAINE 200 mg/1 g
INACTIVE INGREDIENTS: POLYETHYLENE GLYCOL 400 349 mg/1 g; SACCHARIN SODIUM 12 mg/1 g; CHERRY 439 mg/1 g

HurriCaine Spray
Original Wild Cherry

Active ingredient

Benzocaine 20%

Purpose

Oral Anesthetic

Uses

for the temporary relief of occasional minor irritation and pain, associated with:

- canker sores
- sore mouth and throat
- minor injury of the mouth and gums
- minor dental proedures
- minor irritation of the mouth and gums caused by dentures or orthodontic appliances

Warnings

Methemoglobinemia warning:Use of this product may cause methemoglobinemia, a serious condition that must be treated promptly because it reduces the amount of oxygen carried in blood. This can occur even if you have used this product before. Stop use and seek immediate medical attention if you or a child in your care develops:
• pale, gray, or blue colored skin (cyanosis)
• headache
• rapid heart rate
• shortness of breath
• dizziness or lightheadedness
• fatigue or lack of energy

Allergy alert: Do not use if you have a history of allergy to local anesthetics such as procaine, butacaine, benzocaine or other "caine" anesthetics.

Flammable. Do not use near fire or flame. Avoid smoking during use.

Sore throat warning: If sore throat is severe, persists for more than 2 days, is accompanied or followed by fever, headache, rash, swelling, nausea, or vomiting, consult a doctor promptly. If sore mouth symptoms do not improve in 7 days, or irritation, pain, or redness persists or worsens, see your dentist or doctor promptly.

Do not use

• for teething
• in children under 2 years of age

When using this product

- avoid spraying in eyes
- do not store at temperature above 49 °C (120 °F)
- do not puncture or incinerate. Contents under pressure.
- use only as directed. Intentional misuse by deliberately concentrating and inhaling the contents can be harmful or fatal.

Keep out of reach of children.

If more than used for pain is accidentally swallowed, get medical help or contact a Poison Control Center immediately.

Directions

- do not exceed recommended dosage
- firmly insert extension tube into spray can valve and ensure it fits securely into the actuator opening
- position the extension tube 1-2 inches from the affected area
- spray 1/2 second (press and immediately release actuator)
- repeat once if necessary
- anesthesia is accomplished in approximately 20 seconds

adults and children 2 years of age and older: Use up to 4 times daily or as directed by a dentist or doctor.

children under 12 years of age: should be supervised in the use of the product.

children under 2 years of age: do not use.

Inactive ingredients

flavor, hydrocarbon propellant (isobutane and propane), polyethylene glycol, sodium saccharin

Questions or comments?

1-800-238-8542

M-F: 8:00 a.m. - 4:30 p.m. ET

Product Label

HurriCaine Spray - Original Wild Cherry 2oz